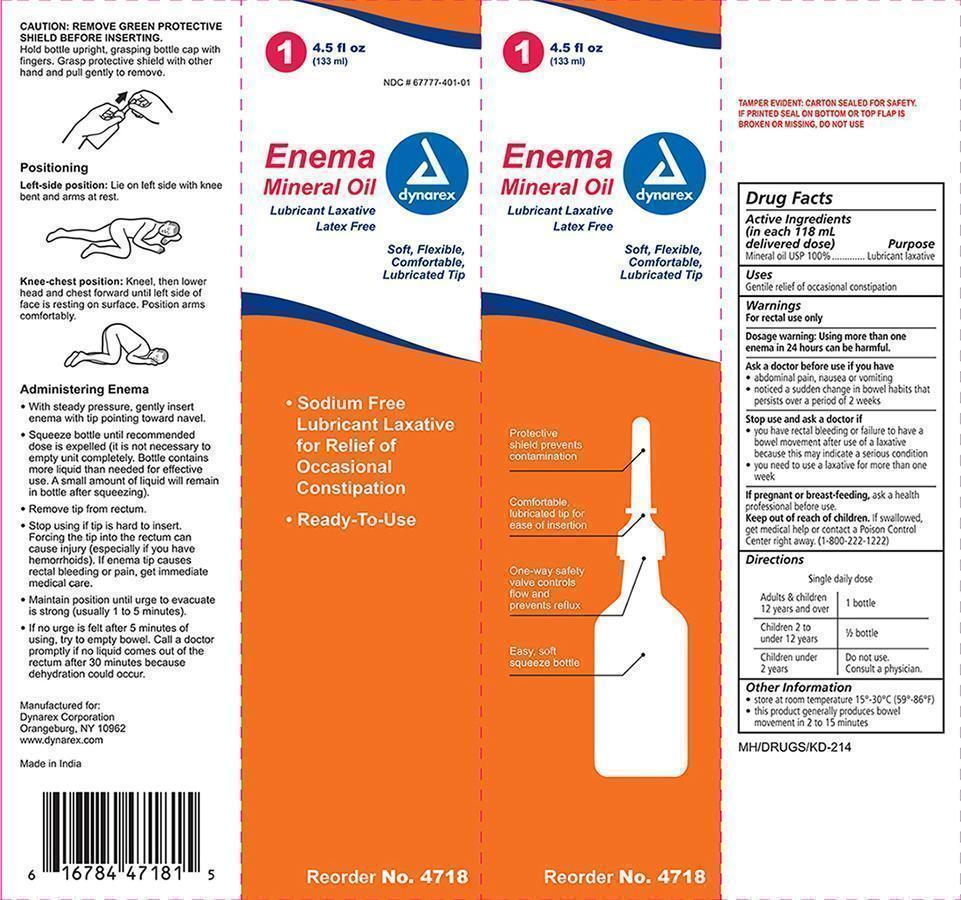 DRUG LABEL: Enema
NDC: 67777-401 | Form: ENEMA
Manufacturer: Dynarex Corporation
Category: otc | Type: HUMAN OTC DRUG LABEL
Date: 20150212

ACTIVE INGREDIENTS: MINERAL OIL 1 mL/1 mL

Enema, Mineral Oil

Active Ingredient Purpose

Mineral Oil, 100% Lubricant Laxative

Uses:

- Gentle relief of occasional constipation

Warnings:

For rectal use only

As a doctor before use if you have:

- abdominal pain, nausea or vomiting
- notice a sudden change in bowel habits that persists over a period of 2 weeks

- If pregnant or breast feeding, ask a health professional before use.

Stop use and ask a doctor if:

- If you have rectal bleeding or failure to have a bowel movement after use of a laxative because this amy indicate a serious condition
- you need to use a laxative for more than one week

Keep out of reach of children

If swallowed, get medical help or contact a Poison Control Center right away. (1-800-222-1222)

Other information:

- Store at room temperature 20 Deg C - 25 Deg C (68 Deg F - 77 Deg F)
- This product produces bowel movement in 2 to 15 minutes

Directions

Single daily dose

Adults and children 12 years and older - 1 bottle

Children 2 to under 12 years - 1/2 bottle

Children under 2 years - Do not use. Consult a physician.

How to use this enema:

REMOVE GREEN PROTECTIVE SHIELD BEFORE INSERTING.

Hold bottle upright, grasping bottle cap with fingers. Grasp protective shield with the other hand and pull gently to remove.

See image on box

Positioning

Left-side position: Lie on left side with knee bent and arms at rest.

See image on box

Knee-chest position: Kneel, then lower head and chest forward until the left side of face is resting on surface. Position arms comfortably.

See image on box

Administering Enema

- With steady pressure, gently insert enema with tip pointing toward navel.
- Squeeze bottle until recommended dose is expelled (it is not necessary to
  empty unit completely. Bottle contains more liquid than needed for effective
  use. A small amount of liquid will remain in bottle after squeezing).
- Remove tip from rectum.
- Stop using if tip is hard to insert. Forcing the tip into the rectum can
  cause injury (especially if you have hemorrhoids). If enema tip causes
  rectal bleeding or pain, get immediatemedical care.
- Maintain position until urge to evacuate is strong (usually 1 to 5 minutes).
- If no urge is felt after 5 minutes of using, try to empty bowel. Call a doctor
  promptly if no liquid comes out of the rectum after 30 minutes because
  dehydration could occur.

Principal Display Panel

Mineral oil enema.jpg